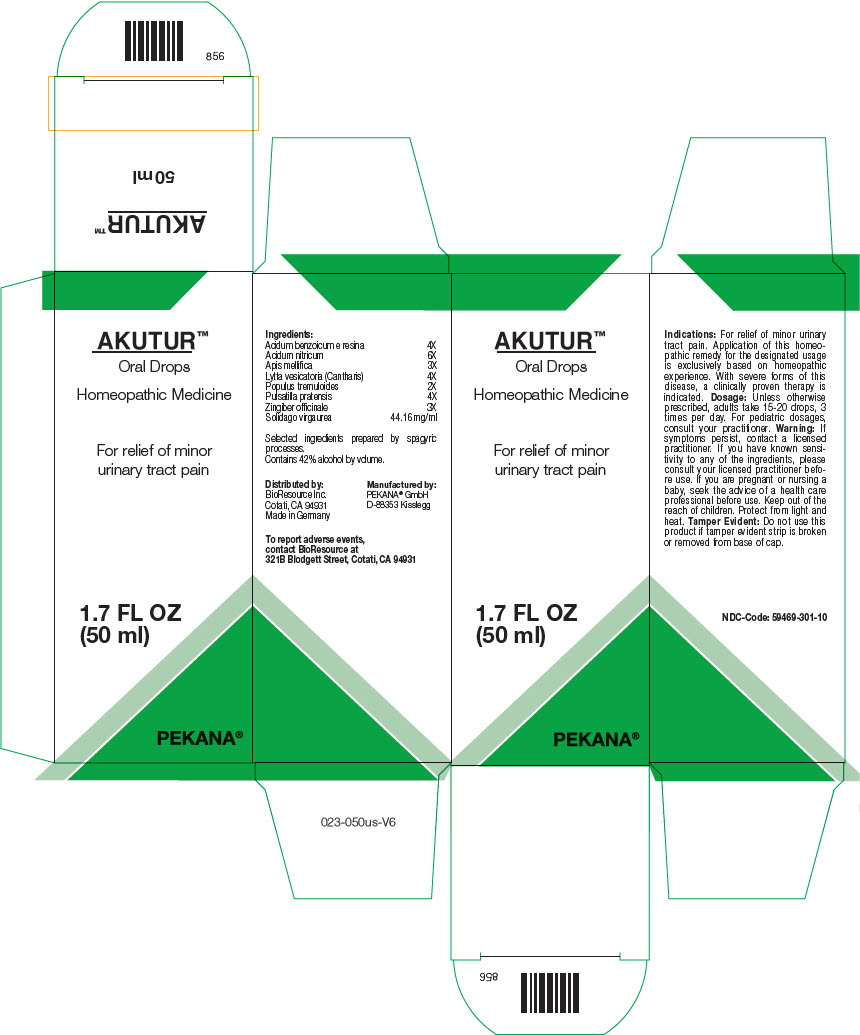 DRUG LABEL: AKUTUR
NDC: 59469-301 | Form: SOLUTION/ DROPS
Manufacturer: PEKANA Nautrheilmittel GmbH
Category: homeopathic | Type: HUMAN OTC DRUG LABEL
Date: 20230111

ACTIVE INGREDIENTS: BENZOIC ACID 4 [hp_X]/50 mL; NITRIC ACID 6 [hp_X]/50 mL; APIS MELLIFERA 3 [hp_X]/50 mL; LYTTA VESICATORIA 4 [hp_X]/50 mL; POPULUS TREMULOIDES BARK 2 [hp_X]/50 mL; PULSATILLA PRATENSIS FLOWERING TOP 4 [hp_X]/50 mL; GINGER 3 [hp_X]/50 mL; SOLIDAGO VIRGAUREA FLOWERING TOP 2208 mg/50 mL
INACTIVE INGREDIENTS: WATER; ALCOHOL

AKUTUR™

ACTIVE INGREDIENT

Ingredients:
Acidum benzoicum e resina | 4X
Acidum nitricum | 6X
Apis mellifica | 3X
Lytta vesicatoria (Cantharis) | 4X
Populus tremuloides | 2X
Pulsatilla pratensis | 4X
Zingiber officinale | 3X
Solidago virgaurea | 44.16 mg/ml

Selected ingredients prepared by spagyric processes.

INACTIVE INGREDIENT

Contains 42% alcohol by volume.

Indications

PURPOSE

For relief of minor urinary tract pain. Application of this homeopathic remedy for the designated usage is exclusively based on homeopathic experience. With severe forms of this disease, a clinically proven therapy is indicated.

Dosage

Unless otherwise prescribed, adults take 15-20 drops, 3 times per day. For pediatric dosages, consult your practitioner.

Warning

If symptoms persist, contact a licensed practitioner. If you have known sensitivity to any of the ingredients, please consult your licensed practitioner before use.

PREGNANCY OR BREAST FEEDING

If you are pregnant or nursing a baby, seek the advice of a health care professional before use.

Keep out of the reach of children.

STORAGE AND HANDLING

Protect from light and heat.

Tamper Evident

Do not use this product if tamper evident strip is broken or removed from base of cap.

QUESTIONS

To report adverse events, contact BioResource at 321B Blodgett Street, Cotati, CA 94931

Distributed by:
BioResource Inc.
Cotati, CA 94931

Manufactured by:
PEKANA® GmbH
D-88353 Kisslegg

PRINCIPAL DISPLAY PANEL - 50 ml Bottle Box

AKUTUR™
Oral Drops

Homeopathic Medicine

For relief of minor
urinary tract pain

1.7 FL OZ
(50 ml)

PEKANA®